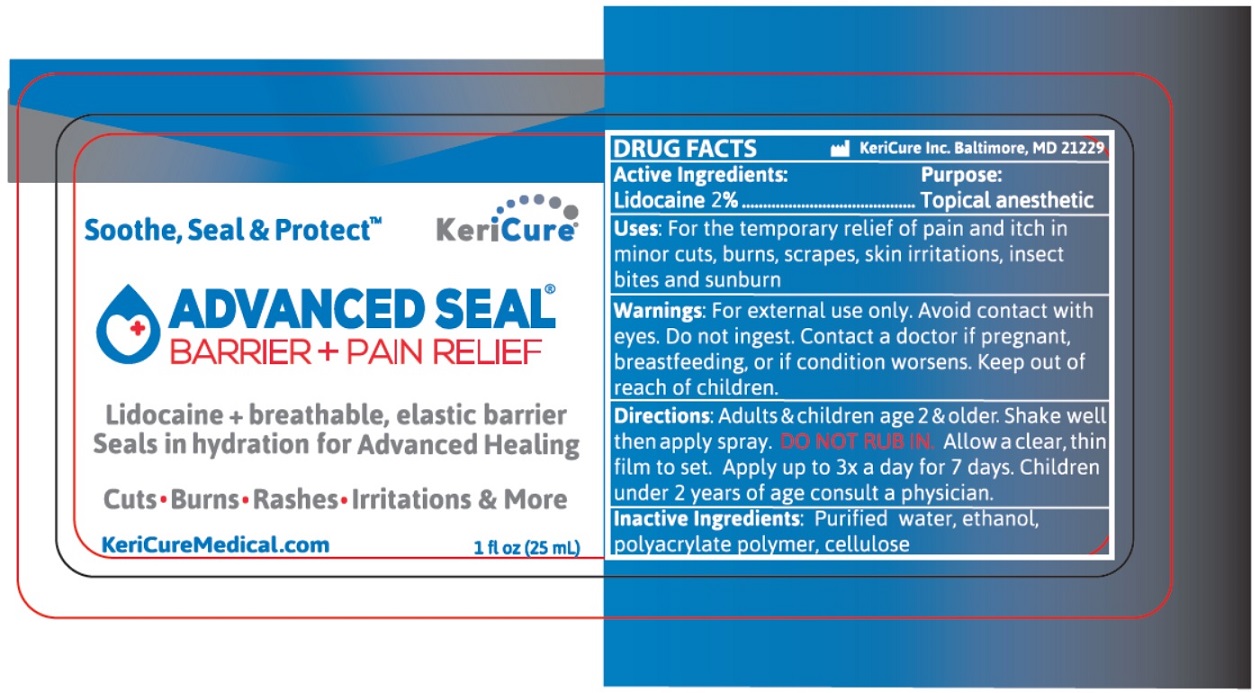 DRUG LABEL: Advanced Seal Barrier plus Pain Relief
NDC: 78280-703 | Form: SPRAY
Manufacturer: Kericure Inc.
Category: otc | Type: HUMAN OTC DRUG LABEL
Date: 20250101

ACTIVE INGREDIENTS: LIDOCAINE 20 mg/1 mL
INACTIVE INGREDIENTS: WATER; ALCOHOL; BUTYL ACRYLATE/METHYL METHACRYLATE/METHACRYLIC ACID COPOLYMER (18000 MW); HYDROXYETHYL CELLULOSE (2000 MPA.S AT 1%)

ADVANCED SEAL® BARRIER + PAIN RELIEF

Active Ingredients:

Lidocaine 2%

Purpose:

Topical anesthetic

INDICATIONS AND USAGE

Uses: For the temporary relief of pain and itch in minor cuts, burns, scrapes, skin irritations, insect bites and sunburn

WARNINGS

Warnings: For external use only. Avoid contact with eyes. Do not ingest. Contact a doctor if pregnant, breastfeeding, or if condition worsens.

Keep out of reach of children.

DOSAGE AND ADMINISTRATION

Directions: Adults & children age 2 & older. Shake well then apply spray. DO NOT RUB IN. Allow a clear, thin film to set. Apply up to 3x a day for 7 days. Children under 2 years of age consult a physician

INACTIVE INGREDIENT

Inactive Ingredients: Purified water, ethanol, polyacrylate polymer, cellulose

Soothe, Seal & ProtectTM

Lidocaine + breathable, elastic barrier

Seals in hydration for Advanced Healing

Cuts • Burns • Rashes • Irritation & More

KeriCureMedical.com

KeriCure Inc. Baltimore, MD 21229